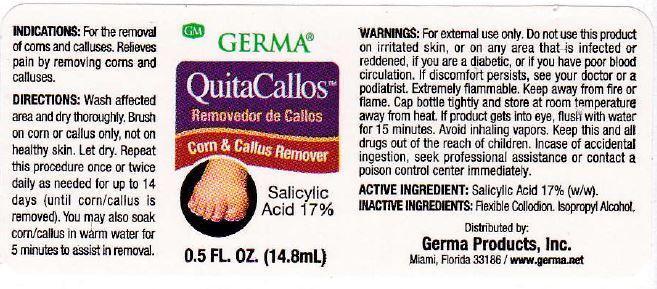 DRUG LABEL: QuitaCallos
NDC: 10095-006 | Form: CREAM
Manufacturer: World Perfumes, Inc
Category: otc | Type: HUMAN OTC DRUG LABEL
Date: 20150505

ACTIVE INGREDIENTS: SALICYLIC ACID 17 g/100 g
INACTIVE INGREDIENTS: PYROXYLIN; ETHER; ALCOHOL; ISOPROPYL ALCOHOL

ACTIVE INGREDEINT: Salicylic Acid 17% (w/w)

PURPOSE

Corn & Callus Remover

KEEP OUT OF REACH OF CHILDREN

Keep this and all drugs out of the reach of children.

INDICATIONS AND USAGE

QuitaCallos

Removedor de Callos

Corn & Callus Remover

Salicylic Acid 17%

DOSAGE AND ADMINISTRATION

Directions: Wash affected area and dry thoroughly. Brush on corn or callus only, not on healthy skin. Let dry. Repeat this procedure once or twice daily as needed for up to 14 days (until corn/callus is removed). You may also soak corn/callus in warm water for 5 minutes to assist in removal.

WARNINGS

Warnings: For external use only. Do not use this product on irritated skin, or on any area that is infected or reddened, if you are a diabetic, or if you have poor blood circulation. If discomfort persists, see your doctor or a podiatrist. Extremely flammable. Keep away from fire or flame. Cap bottle tightly and store at room temperature away from heat. If product gets into eye, flush with water for 15 minutes. Avoid inhaling vapors.

Inactive Ingredients: flexible collodion, isopropyl alcohol.